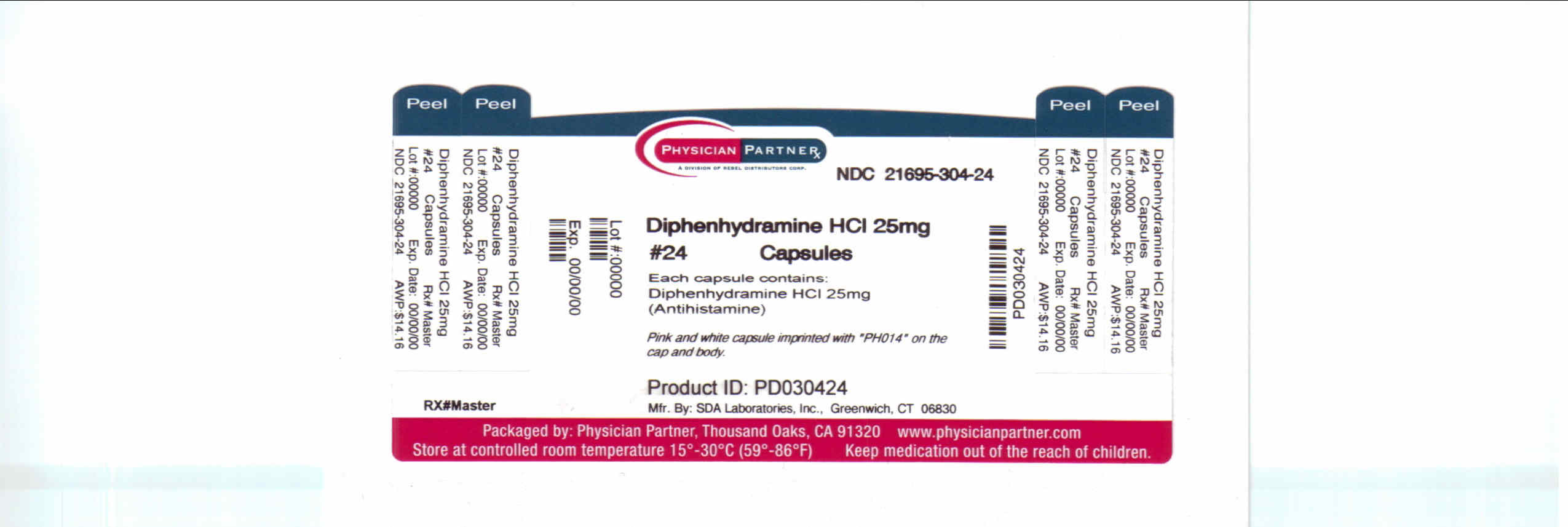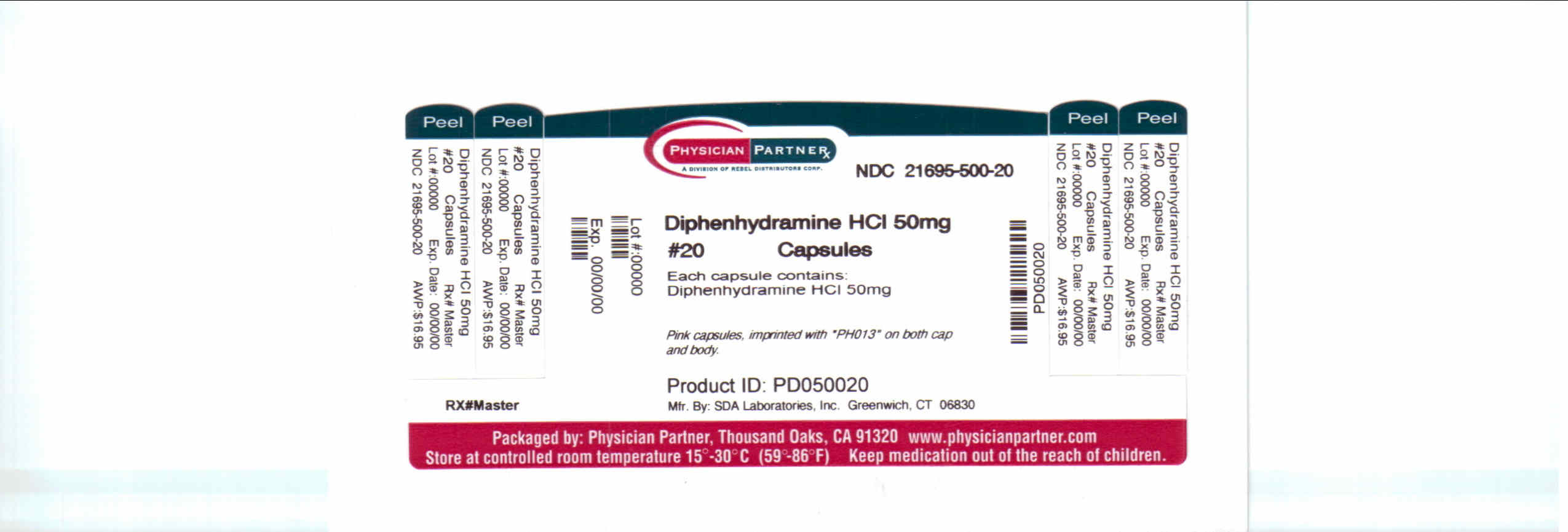 DRUG LABEL: Diphenhydramine
NDC: 21695-304 | Form: CAPSULE
Manufacturer: Rebel Distributors Corp
Category: otc | Type: HUMAN OTC DRUG LABEL
Date: 20110215

ACTIVE INGREDIENTS: DIPHENHYDRAMINE HYDROCHLORIDE 25 mg/1 1
INACTIVE INGREDIENTS: LACTOSE MONOHYDRATE; SILICON DIOXIDE; MAGNESIUM STEARATE; FERROSOFERRIC OXIDE; GELATIN; SODIUM LAURYL SULFATE; D&C RED NO. 28; FD&C RED NO. 40; FD&C BLUE NO. 1

Diphenhydramine Drug Facts

Active ingredient

Diphenhydramine HCl 25mg

Diphenhydramine HCl 50mg

Purpose

Antihistamine

Uses

Temporarily relieves: ° hay fever or other upper respiratory allergies like: ° runny nose

° sneezing ° watery eyes ° itchy nose or throat

Warnings

Do not use with any other product containing Diphenhydramine HCl, including one applied topically.

Ask a doctor or pharmacist before use if you have ° trouble urinating due to enlarged prostate gland ° a breathing problem such as emphysema or chronic bronchitis ° glaucoma ° if you are taking sedatives or tranquilizers

When using this product ° avoid alcoholic drinks ° marked drowsiness may occur ° excitability may occur, especially in children ° alcohol, sedatives & tranquilizers may increase drowsiness ° be careful when driving a motor vehicle or operating machinery.

If pregnant or breast-feeding, ask a health professional before use.

In case of overdose, get medical help or contact a Poison Control Center right away.

Directions

° take every 4-6 hours

° do not take more than 6 doses in 24 hours.

Adults & children 12 years & over: 1-2 capsules

Children 6 to under 12 years: 1 capsule

Children under 6: ask a doctor

Other Information

Store at room temperature 15°-30°C (59°-86°F)

Protect from excessive moisture

Inactive ingredients

Lactose Monohydrate, Silicon Dioxide, Magnesium Steareate, Black Iron Oxide, Gelatin, Sodium Lauyl Sulfate, D&C Red No. 28, FD&C Red No. 40, FD&C Blue No. 1.

Distributed by:

SDA Laboratories, Inc.

Greenwich, CT 06830

Repackaged by:

Rebel Distributors Corp

Thousand Oaks, CA 91320